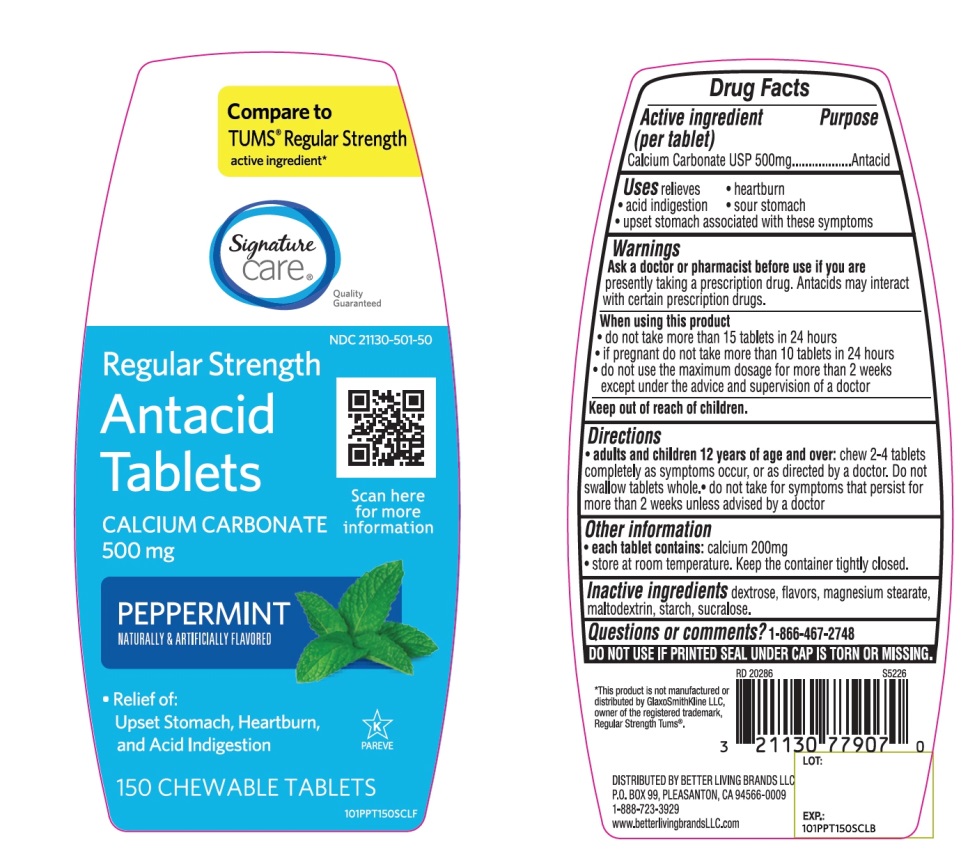 DRUG LABEL: Regular Strength

NDC: 21130-501 | Form: TABLET, CHEWABLE
Manufacturer: SAFEWAY
Category: otc | Type: HUMAN OTC DRUG LABEL
Date: 20251029

ACTIVE INGREDIENTS: CALCIUM CARBONATE 500 mg/1 1
INACTIVE INGREDIENTS: DEXTROSE, UNSPECIFIED FORM; MAGNESIUM STEARATE; MALTODEXTRIN; STARCH, CORN; SUCRALOSE

Regular Strength Antacid Calcium Carbonate Chewable Tablets 150 Count

Active ingredient (per tablet)

Calcium Carbonate USP 500mg

Purpose

Antacid

Uses

relieves

• heartburn

• acid indigestion

• sour stomach

• upset stomach associated with these symptoms

Warnings

Ask a doctor or pharmacist before use if you arepresently taking a prescription drug. Antacids may interact with certain prescription drugs.

When using this product

- do not take more than 15 tablets in 24 hours
- if pregnant do not take more than 10 tablets in 24 hours
- do not use the maximum dosage for more than 2 weeks except under the advice and supervision of a doctor.

Directions

- adults and children 12 years of age and older:chew 2-4 tablets as symptoms occur, or as directed by a doctor
- do not take for symptoms that persist for more than 2 weeks unless advised by a doctor

Other information

- each tablet contains:calcium 200mg
- store at room temperature. Keep the container tightly closed.

Inactive ingredients

dextrose, flavors, magnesium stearate, maltodextrin, starch, sucralose .

Questions?

1-866-467-2748

SAFETY SEALED: DO NOT USE IF PRINTED SEAL UNDER CAP IS TORN OR MISSING

Package/Label Principal Display Panel

NDC 21130-501-50

Compare to Regular Strength Tum® Active Ingredient*

Regular Strength

Antacid Tablets

Calcium Carbonate 500mg/Antacid

Fast Relief of Upset Stomach, Heartburn and Acid Indigestion

Peppermint

Naturally and Artificially Flavored

150 Chewable Tablets

K PAREVE

GLUTEN-FREE

Distributed by:

*This product is not manufactured or distributed by GlaxoSmithKline LLC, owner of the registered trademark, Regular Strength Tums®.